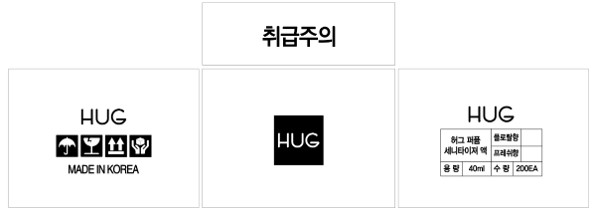 DRUG LABEL: Hug Perfume Sanitizer- Fresh
NDC: 74998-0007 | Form: LIQUID
Manufacturer: CT Cosmetics Co., Ltd
Category: otc | Type: HUMAN OTC DRUG LABEL
Date: 20210202

ACTIVE INGREDIENTS: ALCOHOL 28 mL/40 mL
INACTIVE INGREDIENTS: WATER; ALOE VERA LEAF

CT Cosmetics Co., Ltd - Hug Lets CC Hand Sanitizer Gel(Ethanol)

ACTIVE INGREDIENT

Alcohol

INACTIVE INGREDIENT

Water, Butylene Glycol, Sodium Citrate, Citric Acid, Glycerin, DL-Panthenol, Polysorbate 20, Camellia Sinensis Leaf Extract, Aloe Barbadensis Leaf Extract, Glycyrrhiza Uralensis (Licorice) Root Extract, Rosmarinus Officinalis (Rosemary) Leaf Extract, Flavor

PURPOSE

Sterilization of hands and skin

keep out of reach of the children

INDICATIONS AND USAGE

Spray an appropriate amount on your hand and rub it well to dry it

WARNINGS

For external use only. Flammable. Keep away from heat or flame.

Do not use

- in children less than 2 months of age
- on open skin wounds

When using this product keep out of eyes, ears, and mouth. In case of contact with eyes, rinse thoroughly with water.

Stop use and ask a doctor if irritation or rash occurs. These may be signs of a serious condition.

Keep out of reach of children. If swallowed, get medical help or contact a Poison Control Center right away.

DOSAGE AND ADMINISTRATION

for external use only